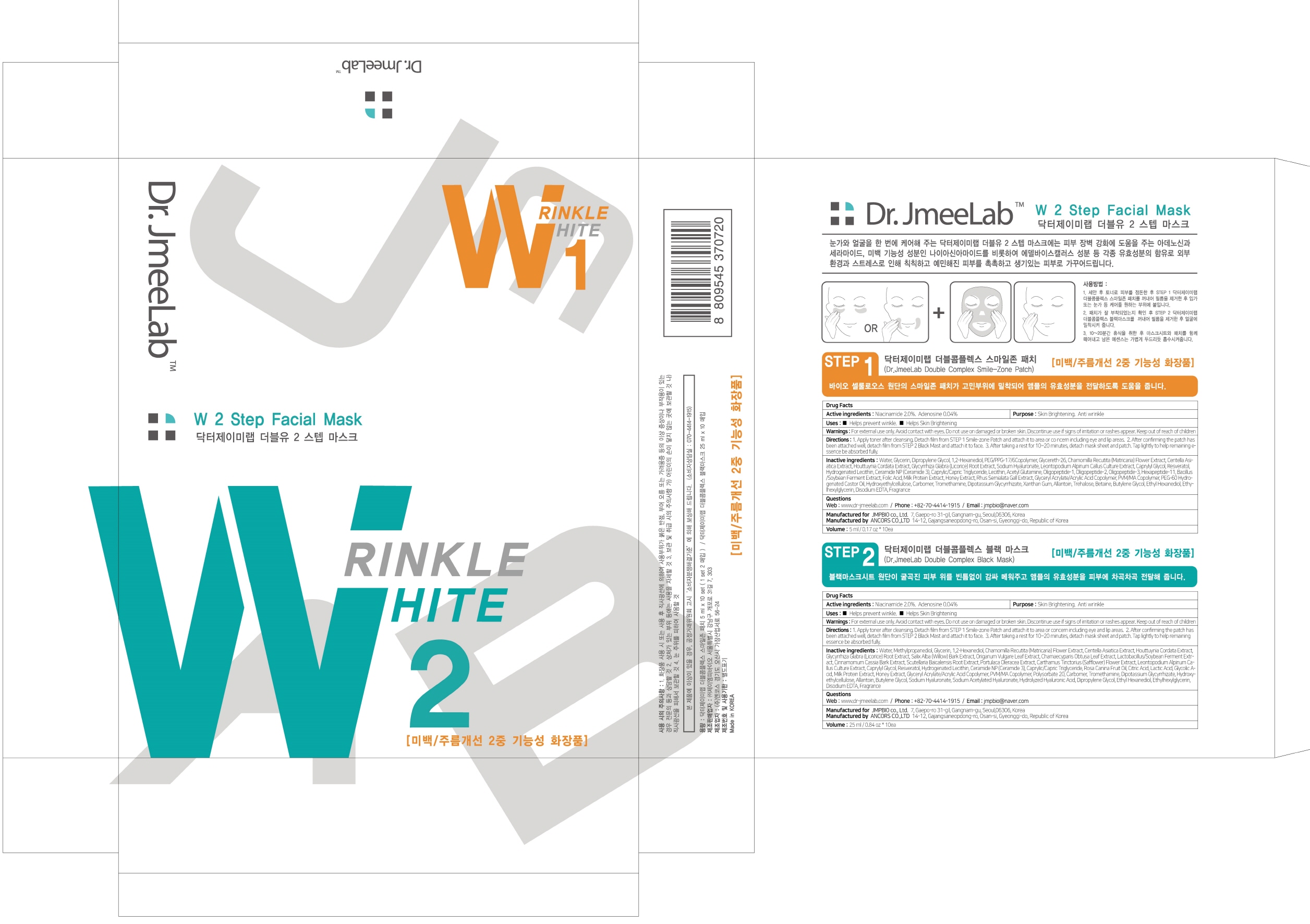 DRUG LABEL: Dr JmeeLab Double Complex Smile Zone
NDC: 72144-030 | Form: PATCH
Manufacturer: JMPBIO co., Ltd.
Category: otc | Type: HUMAN OTC DRUG LABEL
Date: 20181229

ACTIVE INGREDIENTS: Niacinamide 0.10 g/5 mL; Adenosine 0.002 g/5 mL
INACTIVE INGREDIENTS: Water; Glycerin

ACTIVE INGREDIENT

Active ingredients: Niacinamide 2.0%, Adenosine 0.04%

INACTIVE INGREDIENT

Inactive ingredients:

Water, Glycerin, Dipropylene Glycol, 1,2-Hexanediol, PEG/PPG-17/6Copolymer, Glycereth-26, Chamomilla Recutita (Matricaria) Flower Extract, Centella Asiatica Extract, Houttuynia Cordata Extract, Glycyrrhiza Glabra (Licorice) Root Extract, Sodium Hyaluronate, Leontopodium Alpinum Callus Culture Extract, Caprylyl Glycol, Resveratol, Hydrogenated Lecithin, Ceramide NP (Ceramide 3), Caprylic/Capric Triglyceride, Lecithin, Acetyl Glutamine, Oligopeptide-1, Oligopeptide-2, Oligopeptide-3, Hexapeptide-11, Bacillus/Soybean Ferment Extract, Folic Acid, Milk Protein Extract, Honey Extract, Rhus Semialata Gall Extract, Glyceryl Acrylate/Acrylic Acid Copolymer, PVM/MA Copolymer, PEG-60 Hydrogenated Castor Oil, Hydroxyethylcellulose, Carbomer, Tromethamine, Dipotassium Glycyrrhizate, Xanthan Gum, Allantoin, Trehalose, Betaine, Butylene Glycol, Ethyl Hexanediol, Ethylhexylglycerin, Disodium EDTA, Fragrance

PURPOSE

Purpose: Skin Brightening, Anti wrinkle

WARNINGS

For external use only Avoid contact with eyes. Do not use on damaged or broken skin. Discontinue use if signs of irritation or rashes appear. Keep out of reach of children

KEEP OUT OF REACH OF CHILDREN

Uses

- Helps prevent winkle

- Helps Skin Brightening

Directions

1. Apply toner after cleansing. Detach film from STEP 1 Smile-zone Patch and attach it to area or concern including eye and lip areas.

2. After confirming the patch has been attached well, detach film from STEP 2 Black Mast and attach it to face.

3. After taking a rest for 10~20 minutes, detach mask sheet and patch. Tap lightly to help remaining essence be absorbed fully.